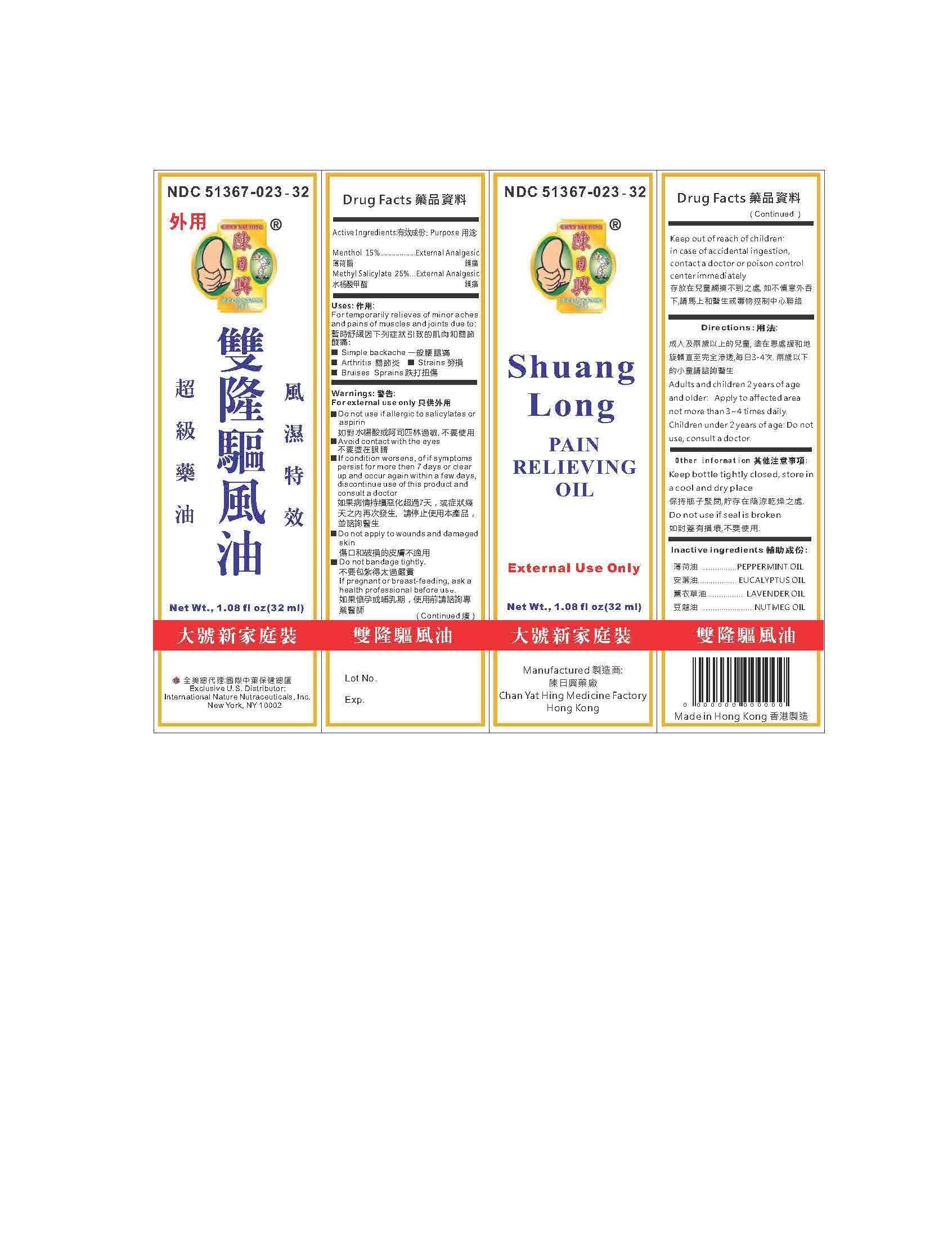 DRUG LABEL: Shuang Long Pain Relieving Oil
NDC: 51367-023 | Form: OIL
Manufacturer: International Nature Nutraceuticals, Inc.
Category: otc | Type: HUMAN OTC DRUG LABEL
Date: 20141126

ACTIVE INGREDIENTS: MENTHOL 4.3 g/1 1; METHYL SALICYLATE 9.4 g/1 1
INACTIVE INGREDIENTS: PEPPERMINT OIL; EUCALYPTUS OIL; LAVENDER OIL; NUTMEG OIL

Drug Listing

Active Ingedients

Menthol 15%

Methyl Salicylate 25%

Uses

For temporary relief of minor aches and pains of muscles and joints due to

- Simple backache
- arthritis
- bruises
- sprains

Warnings

For external use only

Do not use if allergic to salicylates or aspirin

Do not bandage tightly

Do not apply to wounds or damaged skin

During use

Avoid contact with eyes

If pregnant or breast-feeding

Ask a healthcare professional before use

Ask a doctor

If condition worsens, or if symptoms persist for more than 7 days or clear up and occur again within a few days, discontinue use of this product and consult a doctor

Keep out of reach of children

In case of accidental ingestion, contact a doctor or poision control center immediately

Other information

Keep bottle tightly closed, store in a cool and dry place

DO not use if seal is broken

Directions

Adults and children 2 years of age and older: apply to affected area not more than 3-4 times daily

Children under 2 years of age: do not use, consult a doctor

Inactive Ingredients

Peppermint oil, eycalyptus oil, lavender oil, nutmeg oil